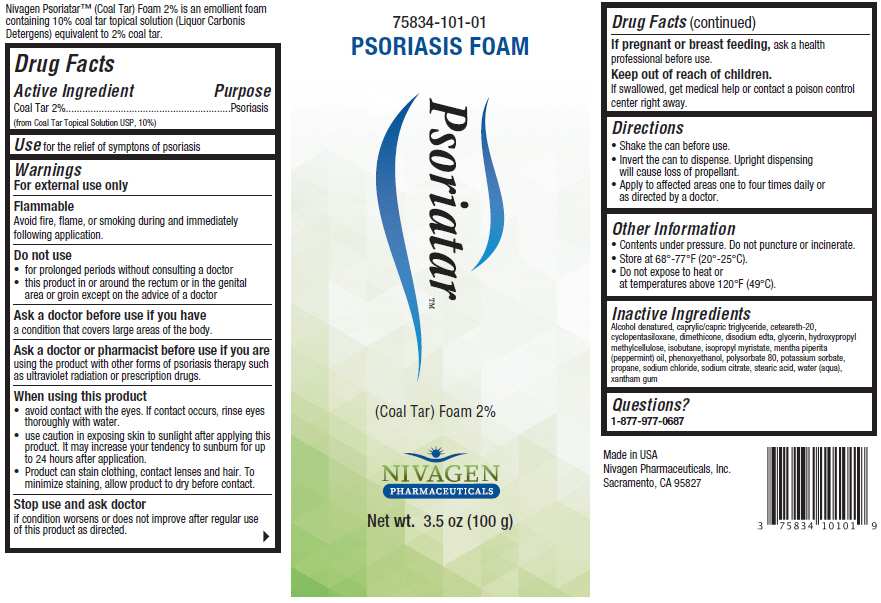 DRUG LABEL: Psoriatar (Coal Tar)
NDC: 75834-101 | Form: AEROSOL, FOAM
Manufacturer: Nivagen Pharmaceuticals, Inc.
Category: otc | Type: HUMAN OTC DRUG LABEL
Date: 20160505

ACTIVE INGREDIENTS: Coal Tar 20 mg/1 g
INACTIVE INGREDIENTS: Isopropyl Alcohol; Medium-Chain Triglycerides; Polyoxyl 20 Cetostearyl Ether; Cyclomethicone 5; Dimethicone; Edetate Disodium; Glycerin; Hypromelloses; Isobutane; Isopropyl Myristate; Peppermint Oil; Phenoxyethanol; Polysorbate 80; Potassium Sorbate; Propane; Sodium Chloride; Sodium Citrate, Unspecified Form; Stearic Acid; Water; Xanthan Gum

Psoriatar™ (Coal Tar) Foam, 2% coal tar foam

Drug Facts

Active Ingredient

Coal Tar 2% (from Coal Tar Topical Solution USP, 10%)

Purpose

Psoriasis

Use

for the relief of symptons of psoriasis

Warnings

For external use only

Flammable

Avoid fire, flame, or smoking during and immediately following application.

Do not use

- for prolonged periods without consulting a doctor
- this product in or around the rectum or in the genital area or groin except on the advice of a doctor

Ask a doctor before use if you have a condition that covers large areas of the body.

Ask a doctor or pharmacist before use if you are using the product with other forms of psoriasis therapy such as ultraviolet radiation or prescription drugs.

When using this product

- avoid contact with the eyes. If contact occurs, rinse eyes thoroughly with water.
- use caution in exposing skin to sunlight after applying this product. It may increase your tendency to sunburn for up to 24 hours after application.
- Product can stain clothing, contact lenses and hair. To minimize staining, allow product to dry before contact.

Stop use and ask doctor if condition worsens or does not improve after regular use of this product as directed.

PREGNANCY OR BREAST FEEDING

If pregnant or breast feeding, ask a health professional before use.

Keep out of reach of children.

If swallowed, get medical help or contact a poison control center right away.

Directions

- Shake the can before use.
- Invert the can to dispense. Upright dispensing will cause loss of propellant.
- Apply to affected areas one to four times daily or as directed by a doctor.

Other Information

- Contents under pressure. Do not puncture or incinerate.
- Store at 68°-77°F (20°-25°C).
- Do not expose to heat or at temperatures above 120°F (49°C).

Inactive Ingredients

Alcohol denatured, caprylic/capric triglyceride, ceteareth-20, cyclopentasiloxane, dimethicone, disodium edta, glycerin, hydroxypropyl methylcellulose, isobutane, isopropyl myristate, mentha piperita (peppermint) oil, phenoxyethanol, polysorbate 80, potassium sorbate, propane, sodium chloride, sodium citrate, stearic acid, water (aqua), xantham gum

Questions?

1-877-977-0687

PRINCIPAL DISPLAY PANEL - 100 g Can Label

75834-101-01
PSORIASIS FOAM

Psoriatar™

(Coal Tar) Foam 2%

NIVAGEN
PHARMACEUTICALS

Net wt. 3.5 oz (100 g)